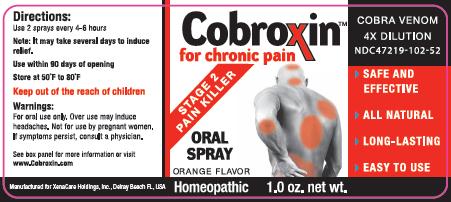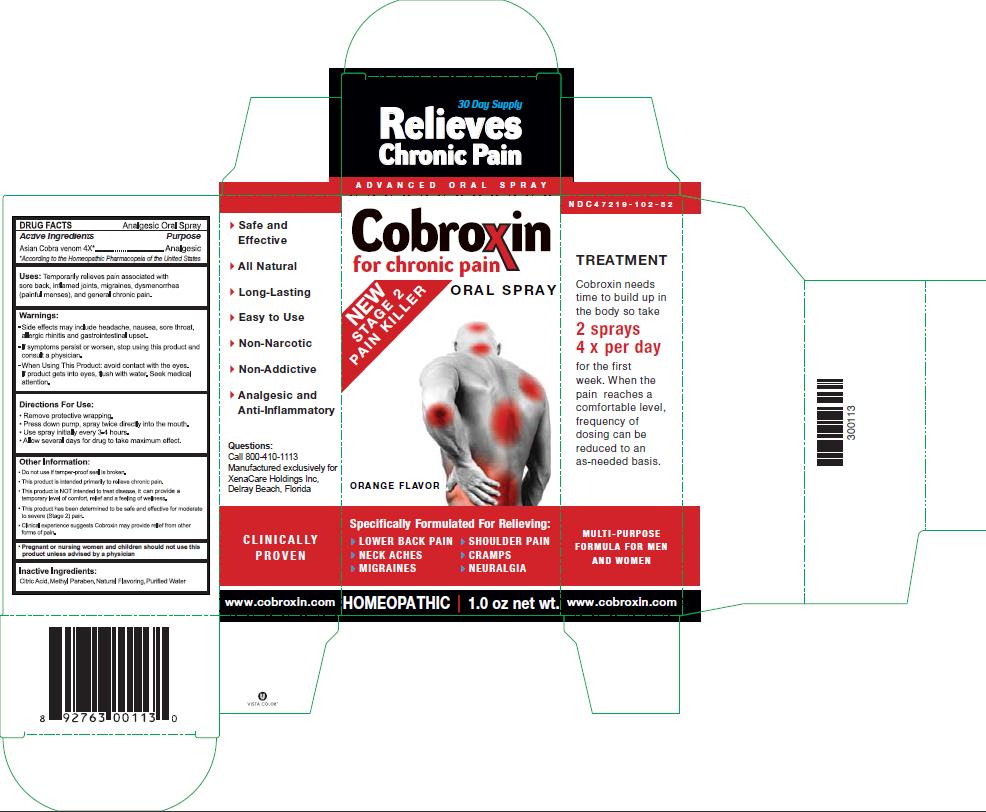 DRUG LABEL: COBROXIN
NDC: 47219-102 | Form: SPRAY, METERED
Manufacturer: RECEPTOPHARM INC
Category: homeopathic | Type: HUMAN OTC DRUG LABEL
Date: 20091103

ACTIVE INGREDIENTS: NAJA NAJA VENOM .043 mg/1 mL
INACTIVE INGREDIENTS: ANHYDROUS CITRIC ACID; ANHYDROUS TRISODIUM CITRATE; METHYLPARABEN; XYLITOL; 2-(DIETHYLAMINO)ETHANOL

DRUG FACTS

Active Ingredients

Asian Cobra venom 4X [According to the Homeopathic Pharmacopeia of the United States]

Purpose

Analgesic

INDICATIONS AND USAGE

Uses: Temporarily relieves pain associated with sore back, inflamed joints, migraines, dysmenorrhea (painful menses), and general chronic pain.

Warnings:

- Side effects may include headahce, nausea, sore throat, allergic rhinitis and gastointestinal upset.
- If symptoms persist or worsen, stop using this product and consult a physician.

- When Using This Product: avoid contact with the eyes. If product gets into eyes, flush with water. Seek medical attention.

Directions For Use:

- Remove protective wrapping.
- Press down pump, spray twice directly into the mouth.
- Use spray intially every 3-4 hours.
- Allow several days for drug to take maximum effect.

Other Information:

- Do not use if tamper-proof seal is broken.
- This product is intended primarily to relieve chronic pain.
- This product is NOT intended to treat disease. It can provide a temporary level of comfort, relief and a feeling of wellness.
- This product has been determined to be safe and effective for moderate to severe (Stage 2) pain.
- Clinical experience suggests Cobroxin may provide relief from other forms of pain.

Pregnant or nursing women and children should not use this product unless advised by a physician

Inactive Ingredients:

Citric Acid, Methyl Paraben, Natural Flavoring, Purified Water

PACKAGE LABEL

Package Label - Principal Display Panel – 1.0 oz Spray Label

PACKAGE LABEL

Package Label - Principal Display Panel – 1.0 oz Spray Carton